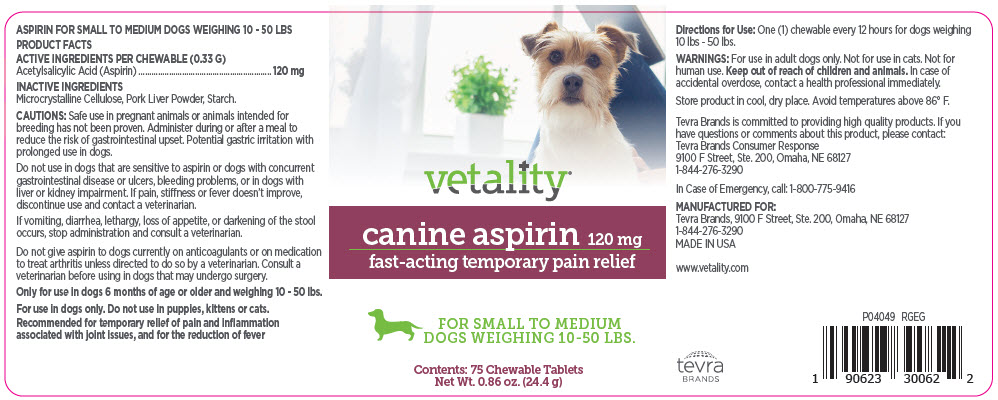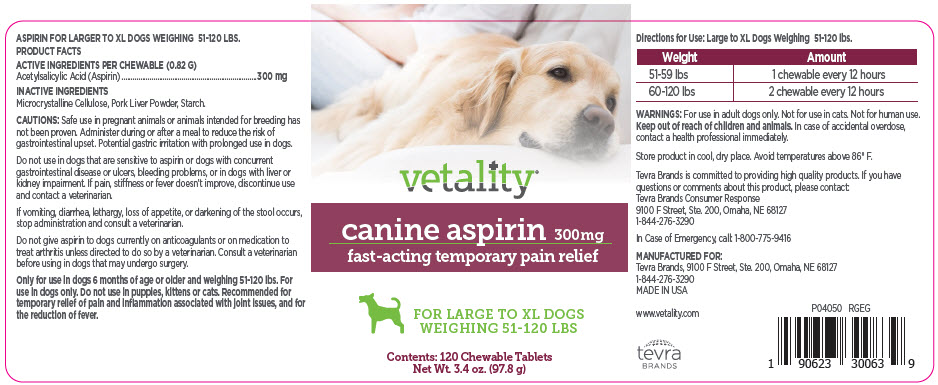 DRUG LABEL: vetality
NDC: 81196-001 | Form: TABLET, CHEWABLE
Manufacturer: Tevra Brands LLC
Category: animal | Type: OTC ANIMAL DRUG LABEL
Date: 20210115

ACTIVE INGREDIENTS: ASPIRIN 120 mg/1 1
INACTIVE INGREDIENTS: Microcrystalline Cellulose; Pork Liver, Cooked; Butylated Hydroxyanisole; Propyl Gallate; Anhydrous Citric Acid; Starch, corn

vetality®

VETERINARY INDICATIONS

ASPIRIN FOR SMALL TO MEDIUM DOGS WEIGHING 10 - 50 LBS

PRODUCT FACTS

ACTIVE INGREDIENTS PER CHEWABLE (0.33 G)

Acetylsalicylic Acid (Aspirin) | 120 mg

INACTIVE INGREDIENTS

Microcrystalline Cellulose, Pork Liver Powder, Starch.

INFORMATION FOR OWNERS/CAREGIVERS

CAUTIONS: Safe use in pregnant animals or animals intended for breeding has not been proven. Administer during or after a meal to reduce the risk of gastrointestinal upset. Potential gastric irritation with prolonged use in dogs.

Do not use in dogs that are sensitive to aspirin or dogs with concurrent gastrointestinal disease or ulcers, bleeding problems, or in dogs with liver or kidney impairment. If pain, stiffness or fever doesn't improve, discontinue use and contact a veterinarian.

If vomiting, diarrhea, lethargy, loss of appetite, or darkening of the stool occurs, stop administration and consult a veterinarian.

Do not give aspirin to dogs currently on anticoagulants or on medication to treat arthritis unless directed to do so by a veterinarian. Consult a veterinarian before using in dogs that may undergo surgery.

Only for use in dogs 6 months of age or older and weighing 10 - 50 lbs.

For use in dogs only. Do not use in puppies, kittens or cats.

Recommended for temporary relief of pain and inflammation associated with joint issues, and for the reduction of fever

DOSAGE AND ADMINISTRATION

Directions for Use: One (1) chewable every 12 hours for dogs weighing 10 lbs - 50 lbs.

SAFE HANDLING WARNING

WARNINGS: For use in adult dogs only. Not for use in cats. Not for human use. Keep out of reach of children and animals. In case of accidental overdose, contact a health professional immediately.

STORAGE AND HANDLING

Store product in cool, dry place. Avoid temperatures above 86° F.

Tevra Brands is committed to providing high quality products. If you have questions or comments about this product, please contact:
Tevra Brands Consumer Response
9100 F Street, Ste. 200, Omaha, NE 68127
1-844-276-3290

In Case of Emergency, call: 1-800-775-9416

MANUFACTURED FOR:
Tevra Brands, 9100 F Street, Ste. 200, Omaha, NE 68127
1-844-276-3290
MADE IN USA

www.vetality.com

P04049 RGEG

PRINCIPAL DISPLAY PANEL - 75 Tablet Bottle Label

vetality®

canine aspirin 120 mg
fast-acting temporary pain relief

FOR SMALL TO MEDIUM
DOGS WEIGHING 10-50 LBS.

Contents: 75 Chewable Tablets
Net Wt. 0.86 oz. (24.4 g)

PRINCIPAL DISPLAY PANEL - 120 Tablet Bottle Label

vetality®

canine aspirin 300mg
fast-acting temporary pain relief

FOR LARGE TO XL DOGS
WEIGHING 51-120 LBS

Contents: 120 Chewable Tablets
Net Wt. 3.4 oz. (97.8 g)